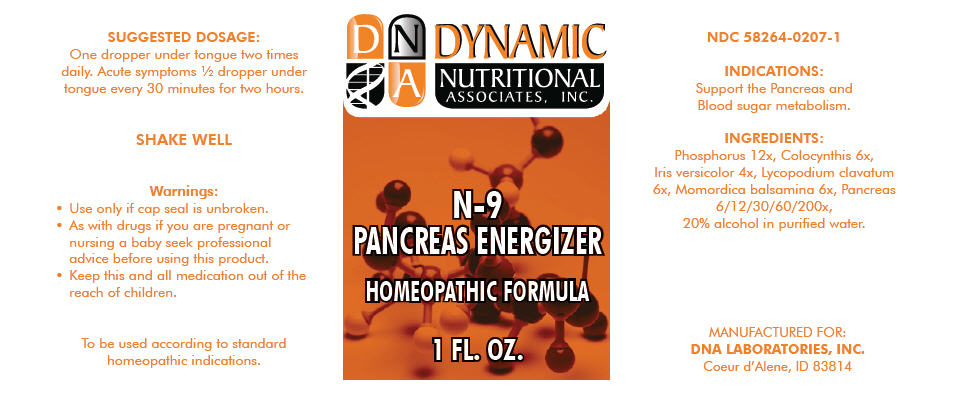 DRUG LABEL: N-9
NDC: 58264-0207 | Form: SOLUTION
Manufacturer: DNA Labs, Inc.
Category: homeopathic | Type: HUMAN OTC DRUG LABEL
Date: 20250109

ACTIVE INGREDIENTS: PHOSPHORUS 12 [hp_X]/1 mL; CITRULLUS COLOCYNTHIS FRUIT PULP 6 [hp_X]/1 mL; IRIS VERSICOLOR WHOLE 4 [hp_X]/1 mL; LYCOPODIUM CLAVATUM WHOLE 6 [hp_X]/1 mL; MOMORDICA BALSAMINA WHOLE 6 [hp_X]/1 mL; BOS TAURUS PANCREAS 200 [hp_X]/1 mL
INACTIVE INGREDIENTS: ALCOHOL; WATER

N-9

NDC 58264-0207-1

INDICATIONS

PURPOSE

Support the Pancreas and Blood sugar metabolism.

ACTIVE INGREDIENT

INGREDIENTS

Phosphorus 12x, Colocynthis 6x, Iris versicolor 4x, Lycopodium clavatum 6x, Momordica balsamina 6x, Pancreas 6/12/30/60/200x, 20% alcohol in purified water.

SUGGESTED DOSAGE

One dropper under tongue two times daily. Acute symptoms ½ dropper under tongue every 30 minutes for two hours.

STORAGE AND HANDLING

SHAKE WELL

Warnings

- Use only if cap seal is unbroken.

PREGNANCY OR BREAST FEEDING

- As with drugs if you are pregnant or nursing a baby seek professional advice before using this product.

KEEP OUT OF REACH OF CHILDREN

- Keep this and all medication out of the reach of children.

To be used according to standard homeopathic indications.

PRINCIPAL DISPLAY PANEL - 1 FL. OZ. Bottle Label

DYNAMIC
NUTRITIONAL
ASSOCIATES, INC.

N-9
PANCREAS ENERGIZER

HOMEOPATHIC FORMULA

1 FL. OZ.